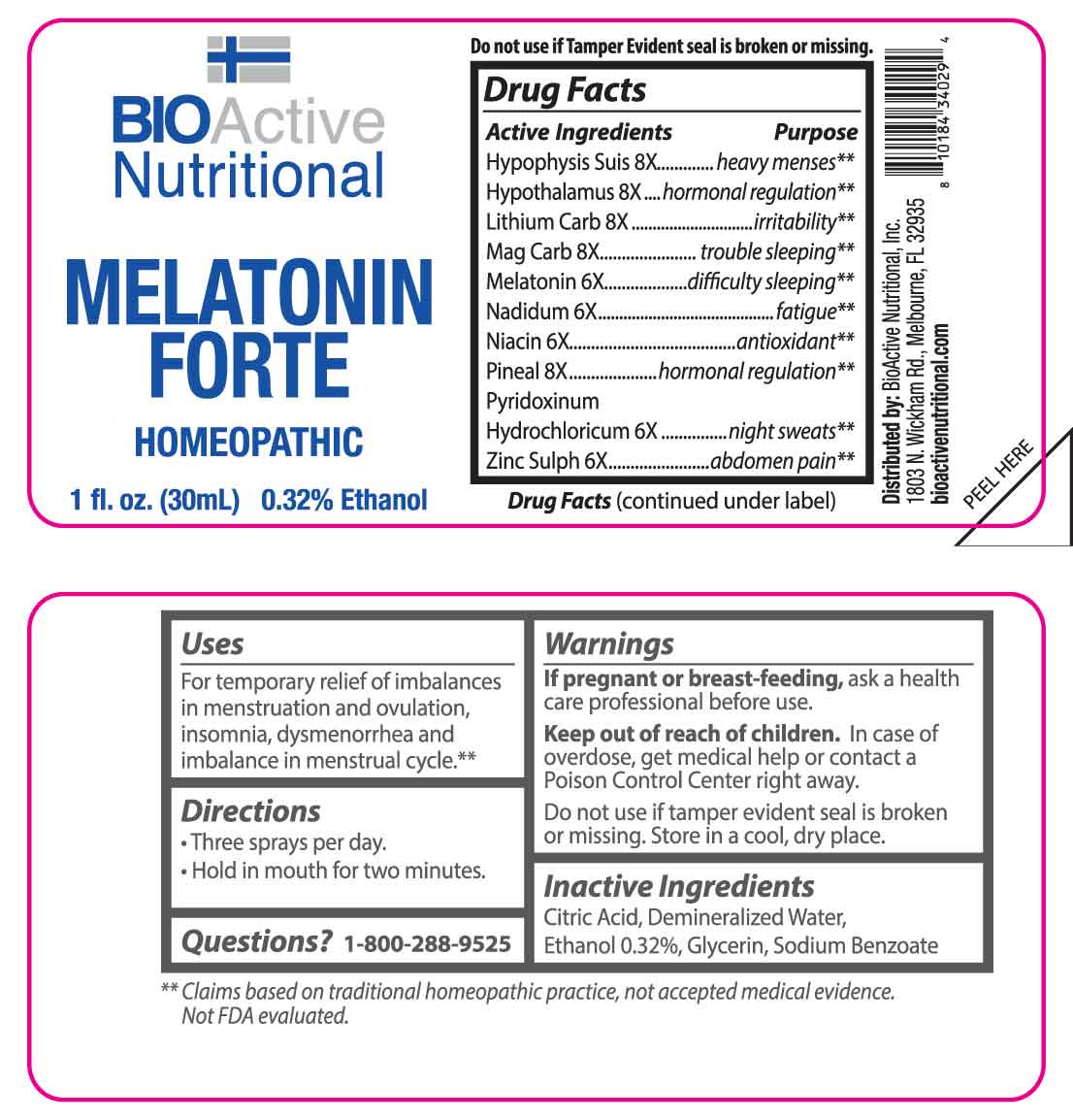 DRUG LABEL: Melatonin Forte
NDC: 43857-0020 | Form: SPRAY
Manufacturer: BioActive Nutritional, Inc.
Category: homeopathic | Type: HUMAN OTC DRUG LABEL
Date: 20250514

ACTIVE INGREDIENTS: MELATONIN 6 [hp_X]/1 mL; NADIDE 6 [hp_X]/1 mL; NIACIN 6 [hp_X]/1 mL; PYRIDOXINE HYDROCHLORIDE 6 [hp_X]/1 mL; ZINC SULFATE HEPTAHYDRATE 6 [hp_X]/1 mL; SUS SCROFA PITUITARY GLAND 8 [hp_X]/1 mL; SUS SCROFA HYPOTHALAMUS 8 [hp_X]/1 mL; LITHIUM CARBONATE 8 [hp_X]/1 mL; MAGNESIUM CARBONATE 8 [hp_X]/1 mL; SUS SCROFA PINEAL GLAND 8 [hp_X]/1 mL
INACTIVE INGREDIENTS: CITRIC ACID MONOHYDRATE; WATER; GLYCERIN; SODIUM BENZOATE; ALCOHOL

DRUG FACTS:

ACTIVE INGREDIENTS:

Hypophysis Suis 8X, Hypothalamus 8X, Lithium Carbonicum 8X, Magnesia Carbonica 8X, Melatonin 6X, Nadidum 6X, Niacin 6X, Pineal 8X, Pyridoxinum Hydrochloricum 6X, Zincum Sulphuricum 6X.

PURPOSE:

Hypophysis Suis – heavy menses,** Hypothalamus – hormonal regulation,** Lithium Carbonicum - irritability,** Magnesia Carbonica – trouble sleeping,** Melatonin – difficulty sleeping,** Nadidum - fatigue,** Niacin - antioxidant,** Pineal – hormonal regulation,** Pyridoxinum Hydrochloricum – night sweats,** Zincum Sulphuricum – abdomen pain**

**Claims based on traditional homeopathic practice, not accepted medical evidence. Not FDA evaluated.

USES:

For temporary relief of imbalances in menstruation and ovulation, insomnia, dysmenorrhea and imbalance in menstrual cycle.**

**Claims based on traditional homeopathic practice, not accepted medical evidence. Not FDA evaluated.

WARNINGS:

If pregnant or breast-feeding, ask a health care professional before use.

Keep out of reach of children. In case of overdose, get medical help or contact a Poison Control Center right away.

Do not use if tamper evident seal is broken or missing.

Store in a cool, dry place.

DIRECTIONS:

• Three sprays per day.

• Hold in mouth for two minutes.

INACTIVE INGREDIENTS:

Citric Acid, Demineralized Water, Ethanol 0.32%, Glycerin, Sodium Benzoate.

KEEP OUT OF REACH OF CHILDREN:

In case of overdose, get medical help or contact a Poison Control Center right away.

QUESTIONS:

Distributed by:
BioActive Nutritional, Inc.
1803 N. Wickham Rd.
Melbourne, FL 32935
bioactivenutritional.com

1-800-288-9525

PACKAGE LABEL DISPLAY:

BIOActive Nutritional

MELATONIN FORTE

HOMEOPATHIC

1 FL OZ (30 ml)